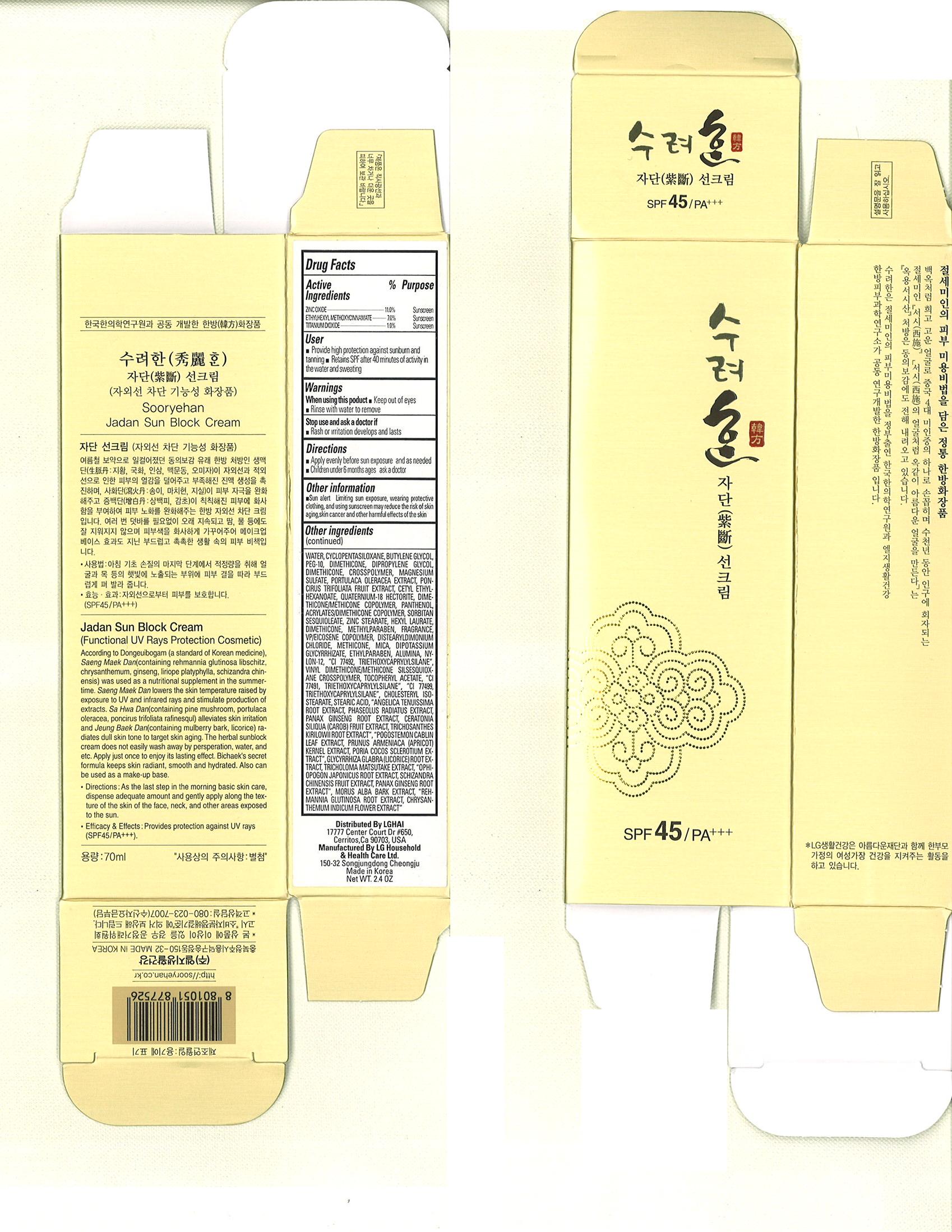 DRUG LABEL: Sooryehan Bichaek Jadan Sun
NDC: 53208-447 | Form: CREAM
Manufacturer: LG Household and Healthcare, Inc.
Category: otc | Type: HUMAN OTC DRUG LABEL
Date: 20100601

ACTIVE INGREDIENTS: ZINC OXIDE 12.88 1/100 mL; TITANIUM DIOXIDE 4.32 mL/100 mL; ENSULIZOLE 3.9 mL/100 mL
INACTIVE INGREDIENTS: WATER; BUTYLENE GLYCOL; CYCLOMETHICONE 5; TROLAMINE; GLYCERIN; DIPROPYLENE GLYCOL; PANTHENOL; MAGNESIUM SULFATE; FILIPENDULA ULMARIA FLOWER; ISOSTEARIC ACID; ZINC STEARATE; METHYLPARABEN; GLYCYRRHIZINATE DIPOTASSIUM; ETHYLPARABEN; ALPHA-TOCOPHEROL ACETATE

Drug Facts

ACTIVE INGREDIENT

ZINC OXIDE 12.88mL/100mL
TITANIUM DIOXIDE 40.32mL/100mL
ENSULIZOLE 3.9mL/100mL

WARNINGS AND PRECAUTIONS

For external use only.

Keep out of reach of children. Is swallowed, get medical help or contact a Poison Control Center right away.

WHEN USING

Keep out of eyes. Rinse with water to remove.

STOP USE

Stop use if a rash or irritation develops and lasts.

PACKAGE LABEL

Sooryehan

Sun Cream

SPF 45 / PA+++